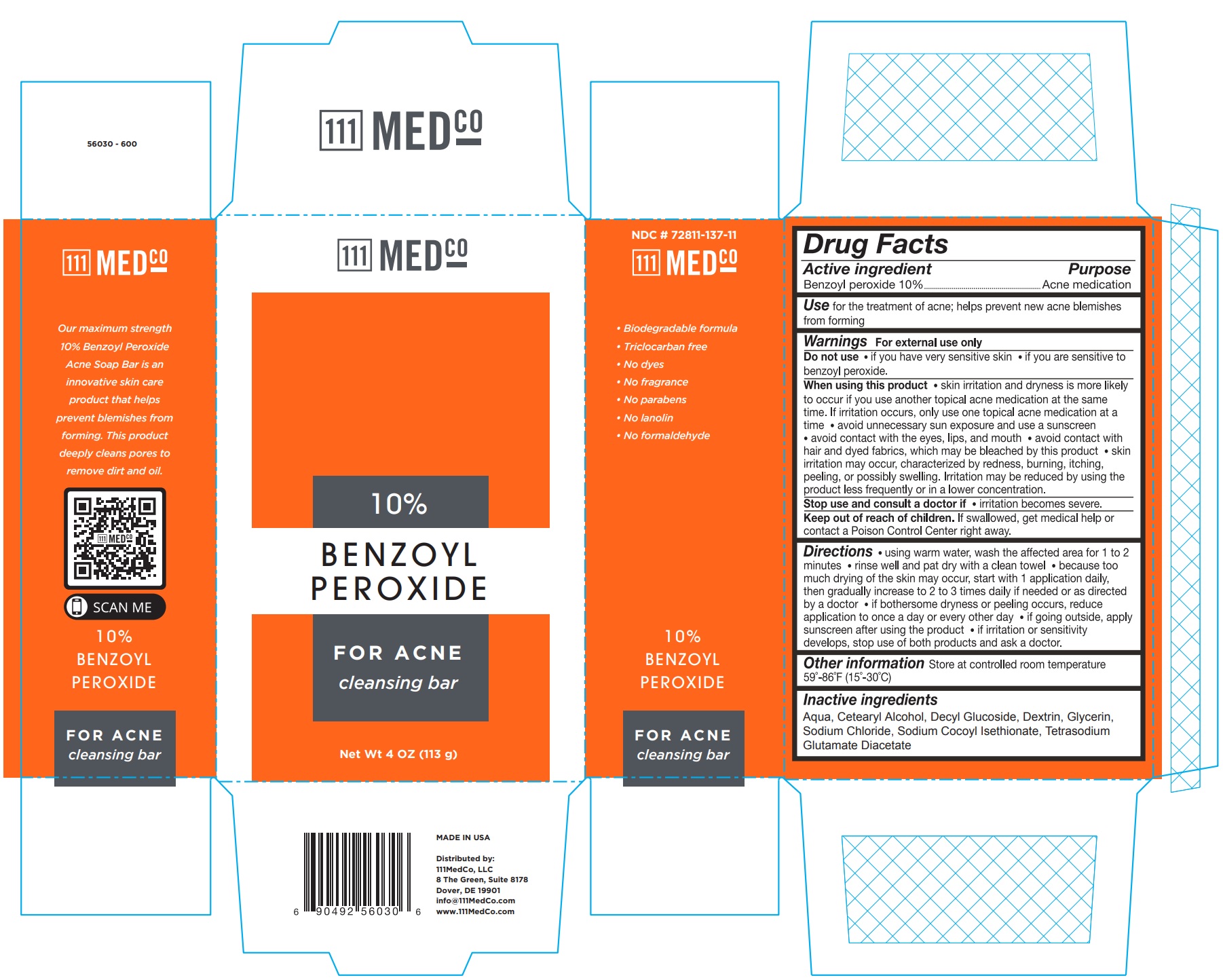 DRUG LABEL: 111 Medco Benzoyl Peroxide
NDC: 72811-137 | Form: SOAP
Manufacturer: 111 Medco
Category: otc | Type: HUMAN OTC DRUG LABEL
Date: 20231212

ACTIVE INGREDIENTS: BENZOYL PEROXIDE 100 mg/1 g
INACTIVE INGREDIENTS: CETOSTEARYL ALCOHOL; SODIUM COCOYL ISETHIONATE; TETRASODIUM GLUTAMATE DIACETATE; WATER; GLYCERIN; SODIUM CHLORIDE; DECYL GLUCOSIDE

111Medco Benzoyl Peroxide Acne Cleansing Bar

Drug Facts

Active ingredient

Benzoyl peroxide 10%

Purpose

Acne medication

INDICATIONS AND USAGE

for the treatment of acne; helps prevent new acne blemishes from forming Use

Warnings

For external use only

Do not use

- if you have very sensitive skin
- if you are sensitive to benzoyl peroxide

When using this product

- skin irritation and dryness is more likely to occur if you use another topical acne medication at the same time. If irritation occurs, only use one topical acne medication at a time
- avoid unnecessary sun exposure and use a sunscreen
- avoid contact with the eyes, lips, and mouth
- avoid contact with hair and dyed fabrics, which may be bleached by this product
- skin irritation may occur, characterized by redness, burning, itching, peeling, or possibly swelling. Irritation may be reduced by using the product less frequently or in a lower concentration.

Stop use and consult a doctor if

- irritation becomes severe.

KEEP OUT OF REACH OF CHILDREN

If swallowed, get medical help or contact a Poison Control Center right away. Keep out of reach of children.

Directions

- using warm water, wash the affected area for 1 to 2 minutes
- rinse well and pat dry with a clean towel
- because too much drying of the skin may occur, start with 1 application daily, then gradually increase to 2 or 3 times daily if needed or as directed by a doctor
- if bothersome dryness or peeling occurs, reduce application to once a day or every other day
- if going outside, apply sunscreen after using the product
- If irritation or sensitivity develops, stop use of both products and ask a doctor.

STORAGE AND HANDLING

Store at controlled room temperature 59° - 86°F (15° - 30°C) Other information

Inactive ingredients

Aqua, Cetearyl Alcohol, Decyl Glucoside, Dextrin, Glycerin, Sodium Chloride, Sodium Cocoyl Isethionate, Tetrasodium Glutamate Diacetate

MADE IN USA

Distributed by:

111MedCo, LLC

8 The Green, Suite 8178

Dover, DE 19901

info@111MedCo.com

www.111MedCo.com

PACKAGE LABEL

111 Medco

10% BENZOYL PEROXIDE

FOR ACNE

cleansing bar

Net Wt 4 OZ (113 g)